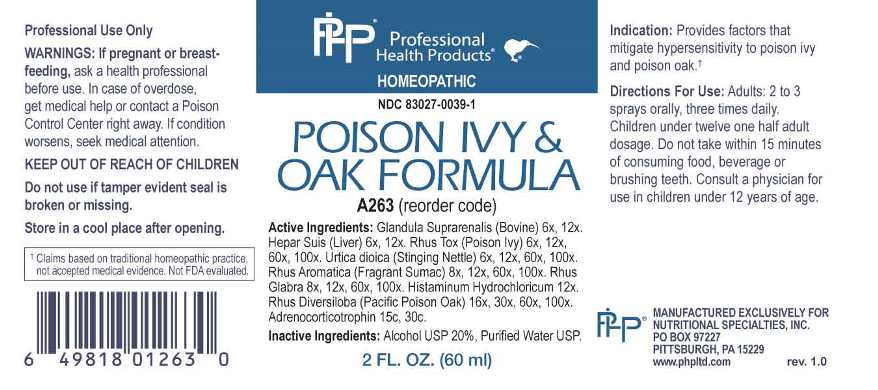 DRUG LABEL: Poison Ivy and Oak Formula
NDC: 83027-0039 | Form: SPRAY
Manufacturer: Nutritional Specialties, Inc.
Category: homeopathic | Type: HUMAN OTC DRUG LABEL
Date: 20240725

ACTIVE INGREDIENTS: BOS TAURUS ADRENAL GLAND 6 [hp_X]/1 mL; PORK LIVER 6 [hp_X]/1 mL; TOXICODENDRON PUBESCENS LEAF 6 [hp_X]/1 mL; URTICA DIOICA WHOLE 6 [hp_X]/1 mL; RHUS AROMATICA ROOT BARK 8 [hp_X]/1 mL; RHUS GLABRA TOP 8 [hp_X]/1 mL; HISTAMINE DIHYDROCHLORIDE 12 [hp_X]/1 mL; TOXICODENDRON DIVERSILOBUM LEAF 16 [hp_X]/1 mL; CORTICOTROPIN 15 [hp_C]/1 mL
INACTIVE INGREDIENTS: WATER; ALCOHOL

DRUG FACTS:

ACTIVE INGREDIENTS:

Glandula Suprarenalis (Bovine) 6X, 12X, Hepar Suis (Liver) 6X, 12X, Rhus Tox (Poison Ivy) 6X, 12X, 60X, 100X, Urtica Dioica (Stinging Nettle) 6X, 12X, 60X, 100X, Rhus Aromatica (Fragrant Sumac) 8X, 12X, 60X, 100X, Rhus Glabra 8X, 12X, 60X, 100X, Histaminum Hydrochloricum 12X, Rhus Diversiloba (Pacific Poison Oak) 16X, 30X, 60X, 100X, Adrenocorticotrophin 15C, 30C.

PURPOSE:

Provides factors that mitigate hypersensitivity to poison ivy and poison oak.

†Claims based on traditional homeopathic practice, not accepted medical evidence. Not FDA evaluated.

WARNINGS:

Professional Use Only

If pregnant or breast-feeding, ask a health professional before use.

In case of overdose, get medical help or contact a Poison Control Center right away.

If condition worsens, seek medical attention.

KEEP OUT OF REACH OF CHILDREN

Do not use if tamper evident seal is broken or missing.

Store in a cool place after opening

KEEP OUT OF REACH OF CHILDREN:

In case of overdose, get medical help or contact a Poison Control Center right away.

DIRECTIONS:

Adults: 2 to 3 sprays orally, three times daily. Children under twelve one half adult dosage. Do not take within 15 minutes of consuming food, beverage or brushing teeth. Consult a physician for use in children under 12 years of age.

INDICATIONS:

Provides factors that mitigate hypersensitivity to poison ivy and poison oak.†
†Claims based on traditional homeopathic practice, not accepted medical evidence. Not FDA evaluated.

INACTIVE INGREDIENTS:

Alcohol USP 20%, Purified Water USP.

QUESTIONS:

MANUFACTURED EXCLUSIVELY FOR

NUTRITIONAL SPECIALTIES, INC.

PO BOX 97227

PITTSBURG, PA 15229

www.phpltd.com

PACKAGE LABEL DISPLAY:

Professional

Health Products

HOMEOPATHIC

NDC 83027-0039-1

POISON IVY &

OAK FORMULA

2 FL. OZ (60 ml)